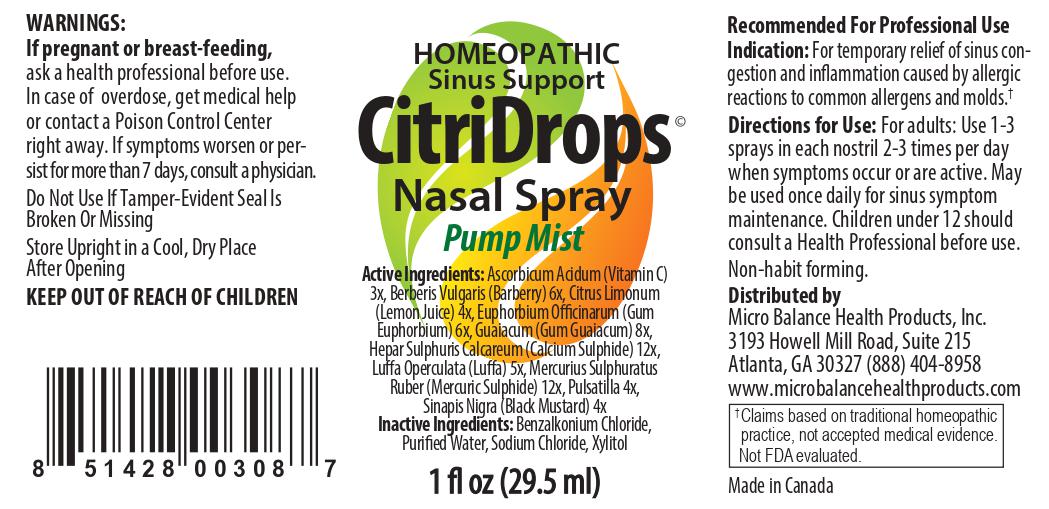 DRUG LABEL: CitriDrops
NDC: 83018-0003 | Form: SPRAY
Manufacturer: Micro Balance Health Products
Category: homeopathic | Type: HUMAN OTC DRUG LABEL
Date: 20230220

ACTIVE INGREDIENTS: LEMON JUICE 4 [hp_X]/1 mL; CALCIUM SULFIDE 12 [hp_X]/1 mL; EUPHORBIA RESINIFERA RESIN 6 [hp_X]/1 mL; BERBERIS VULGARIS ROOT BARK 6 [hp_X]/1 mL; LUFFA OPERCULATA WHOLE 4 [hp_X]/1 mL; PULSATILLA PRATENSIS 4 [hp_X]/1 mL; GUAIAC 8 [hp_X]/1 mL; ASCORBIC ACID 3 [hp_X]/1 mL; MERCURIC SULFIDE 12 [hp_X]/1 mL; BLACK MUSTARD SEED 4 [hp_X]/1 mL
INACTIVE INGREDIENTS: WATER; SODIUM CHLORIDE; BENZALKONIUM CHLORIDE; XYLITOL

CitriDrops Nasal Spray

Active Ingredients:

Ascorbicum Acidum (Vitamin C) 3x, Berberis Vulgaris (Barberry) 6x, Citrus Limonum (Lemon Juice) 4x, Euphorbium Officinarum (Gum Euphorbium) 6x, Guaiacum (Gum Guaiacum) 8x, Hepar Sulphuris Calcareum (Calcium Sulphide) 12x, Luffa Operculata (Luffa) 5x, Mercurius Sulphuratus Ruber (Mercuric Sulphide) 12x, Pulsatilla 4x, Sinapis Nigra (Black Mustard) 4x

Inactive Ingredients:

Benzalkonium Chloride, Purified Water, Sodium Chloride, Xylitol

Recommended For Professional Use Indication:

For temporary relief of sinus congestion and inflammation caused by allergic reactions to common allergens and molds.

INDICATIONS AND USAGE

For temporary relief of sinus congestion and inflammation caused by allergic reactions to common allergens and molds

Directions for Use:

For adults: Use 1-3 sprays in each nostril 2-3 times per day when symptoms occur or are active. May be used once daily for sinus symptom maintenance. Children under 12 should consult a Health Professional before use. Non-habit forming.

WARNINGS

If pregnant or breast-feeding,

ask a health professional before use. In case of overdose, get medical help or contact a Poison Control Center right away. If symptoms worsen or persist for more than 7 days, consult a physician.